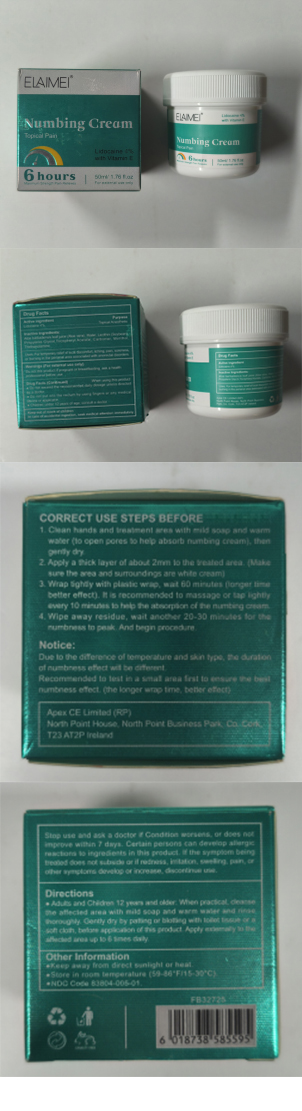 DRUG LABEL: ELAIMEI Numbing Cream
NDC: 83804-005 | Form: CREAM
Manufacturer: Shenzhen Shandian Jingling Technology Co., Ltd.
Category: otc | Type: HUMAN OTC DRUG LABEL
Date: 20250819

ACTIVE INGREDIENTS: LIDOCAINE 4 g/100 mL
INACTIVE INGREDIENTS: WATER; .ALPHA.-TOCOPHEROL ACETATE; ALOE BARBADENSIS LEAF; PROPYLENE GLYCOL; TRIETHANOLAMINE; LECITHIN, SOYBEAN; CARBOMER; MENTHOL

83804-005 ELAIMEI Numbing Cream

ACTIVE INGREDIENT

Lidocaine 4%

PURPOSE

Topical Anesthetic

INDICATIONS AND USAGE

Uses: For temporary relief of local discomfort, itching, pain, sorenessor burning in the perianal area associated with anorectal disorders

WARNINGS

Do not this product if pregnant or breastfeeding, ask a heaith professional before use

DO NOT USE

Do not exceed the recommended daily dosage unless directed by a doctor.
Do nat put into the reclum by using fingers or any medicatd evice or applicator.
Children under 12 years of age, consult a doctor.

WHEN USING

CORRECT USE STEPS BEFORE TATTOOING
1.Clean hands and treatment area with mild soap and warmwater (to open pores to help absorb numbing cream), thengently dry.
2. Apply a thick layer of about 2mm to the treated area. (Makesure the tattoo area and surroundings are white cream)
3. Wrap tightly with plastic wrap, wait 60 minutes (longer fimebetter effect). lt is recommended to massage or tap iightlyevery 10 minutes to help the absorption of the numbing cream.
4.Wipe away residue, wait another 20-30 minutes for thenumbness to peak. And begin procedure.

Stop use and ask a doctor if Condition worsens, or does notimprove within 7 days.Certain persons can develop aliergicreactions to ingredients in this product. if the symptom beingtreated does not subside or if redness, irritation, swelling, pain, orother symptoms develop or increase, discontinue use.

KEEP OUT OF REACH OF CHILDREN SECTION

DOSAGE AND ADMINISTRATION

Adults and Children 12 years and older: When practical, cleansethe affected area with mild soap and warm water and rinsethoroughly, Gently dry by patting or blotting with toitet tissue or aSoft cloth before application of this product. Apply externally to theaffected area up to 6 times daily.

INACTIVE INGREDIENT

Aloe barbadensis leaf juice (Aloe vera)
Water
Lecithin (Soybean)
Propylene Glycol
Tocopheryl Acetate
Carbomer
Menthol
Triethanolamine